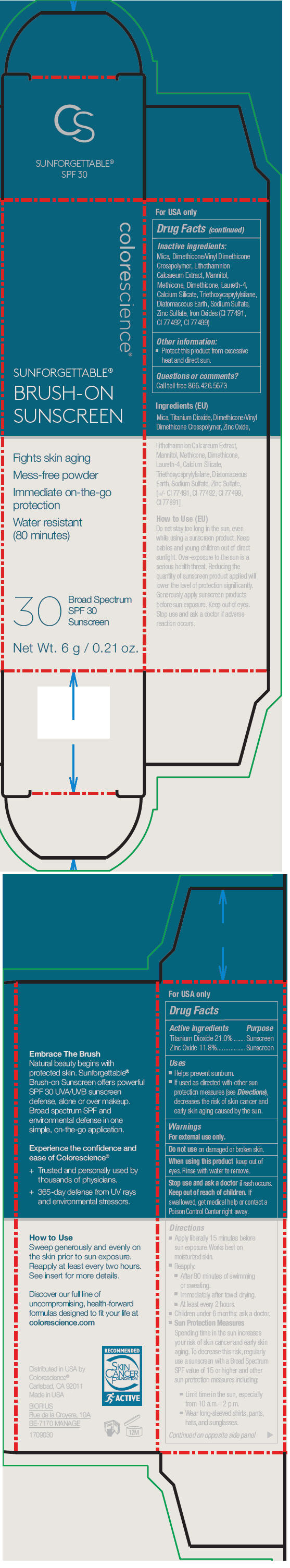 DRUG LABEL: Sunforgettable Brush-On Sunscreen SPF 30
NDC: 68078-021 | Form: POWDER
Manufacturer: Colorescience
Category: otc | Type: HUMAN OTC DRUG LABEL
Date: 20211222

ACTIVE INGREDIENTS: Titanium Dioxide 210 mg/1 g; Zinc Oxide 118 mg/1 g
INACTIVE INGREDIENTS: Mica; Dimethicone/Vinyl Dimethicone Crosspolymer (Soft Particle); Phymatolithon Calcareum; Mannitol; Methicone (20 CST); Dimethicone; Laureth-4; Calcium Silicate; Triethoxycaprylylsilane; Diatomaceous Earth; Sodium Sulfate; Zinc Sulfate, Unspecified Form; FERRIC OXIDE YELLOW; FERRIC OXIDE RED; FERROSOFERRIC OXIDE

Sunforgettable® Brush-On Sunscreen SPF 30

Drug Facts

ACTIVE INGREDIENT

Active ingredients | Purpose
Titanium Dioxide 21.0% | Sunscreen
Zinc Oxide 11.8% | Sunscreen

Uses

- Helps prevent sunburn.
- If used as directed with other sun protection measures (see Directions), decreases the risk of skin cancer and early skin aging caused by the sun.

Warnings

For external use only.

Do not use on damaged or broken skin.

When using this product keep out of eyes. Rinse with water to remove.

Stop use and ask a doctor if rash occurs.

Keep out of reach of children. If swallowed, get medical help or contact a Poison Control Center right away.

Directions

- Apply liberally 15 minutes before sun exposure. Works best on moisturized skin.
- Reapply:
  - After 80 minutes of swimming or sweating.
  - Immediately after towel drying.
  - At least every 2 hours.
- Children under 6 months: ask a doctor.
- Sun Protection Measures
  Spending time in the sun increases your risk of skin cancer and early skin aging. To decrease this risk, regularly use a sunscreen with a Broad Spectrum SPF value of 15 or higher and other sun protection measures including:
  - Limit time in the sun, especially from 10 a.m.– 2 p.m.
  - Wear long-sleeved shirts, pants, hats, and sunglasses.

Inactive ingredients

Mica, Dimethicone/Vinyl Dimethicone Crosspolymer, Lithothamnion Calcareum Extract, Mannitol, Methicone, Dimethicone, Laureth-4, Calcium Silicate, Triethoxycaprylylsilane, Diatomaceous Earth, Sodium Sulfate, Zinc Sulfate, Iron Oxides (CI 77491, CI 77492, CI 77499)

Other information

- Protect this product from excessive heat and direct sun.

Questions or comments?

Call toll free 866.426.5673

Distributed in USA by
Colorescience®
Carlsbad, CA 92011

PRINCIPAL DISPLAY PANEL - 6 g Tube Carton

colorescience®

SUNFORGETTABLE®
BRUSH-ON
SUNSCREEN

Fights skin aging

Mess-free powder

Immediate on-the-go
protection

Water resistant
(80 minutes)

30
Broad Spectrum
SPF 30
Sunscreen

Net Wt. 6 g / 0.21 oz.